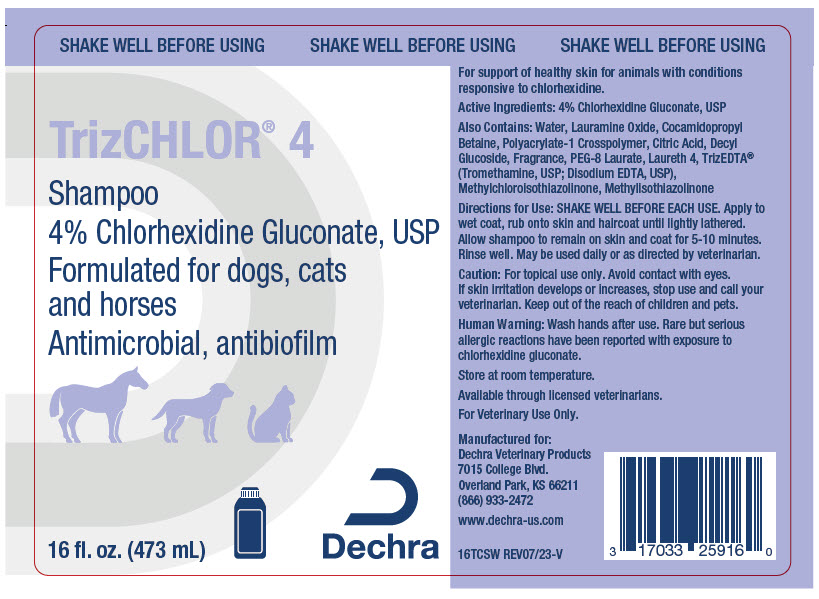 DRUG LABEL: TrizChlor 4
NDC: 17033-259 | Form: SOLUTION
Manufacturer: Dechra Veterinary Products
Category: animal | Type: OTC ANIMAL DRUG LABEL
Date: 20240212

ACTIVE INGREDIENTS: Chlorhexidine Gluconate 40 mg/1 mL

TrizChlor® 4 Shampoo

VETERINARY INDICATIONS

For support of healthy skin for animals with conditions responsive to chlorhexidine.

DESCRIPTION

Active Ingredients: 4% Chlorhexidine Gluconate, USP

Also Contains: Water, Lauramine Oxide, Cocamidopropyl Betaine, Polyacrylate-1 Crosspolymer, Citric Acid, Decyl Glucoside, Fragrance, PEG-8 Laurate, Laureth 4, TrizEDTA® (Tromethamine, USP; Disodium EDTA, USP), Methylchloroisothiazolinone, Methylisothiazolinone

DOSAGE AND ADMINISTRATION

Directions for Use: SHAKE WELL BEFORE EACH USE. Apply to wet coat, rub onto skin and haircoat until lightly lathered. Allow shampoo to remain on skin and coat for 5-10 minutes. Rinse well. May be used daily or as directed by veterinarian.

PRECAUTIONS

Caution: For topical use only. Avoid contact with eyes. If skin irritation develops or increases, stop use and call your veterinarian. Keep out of the reach of children and pets.

SAFE HANDLING WARNING

Human Warning: Wash hands after use. Rare but serious allergic reactions have been reported with exposure to chlorhexidine gluconate.

STORAGE AND HANDLING

Store at room temperature.
Available through licensed veterinarians.

Made in the USA.

Manufactured for: Dechra Veterinary Products
7015 College Blvd., Overland Park, KS 66211
866.933.2472
www.dechra-us.com

16TCSW REV09/20

PRINCIPAL DISPLAY PANEL - 473 mL Bottle Label

SHAKE WELL BEFORE USING

TrizCHLOR® 4
Shampoo
4% Chlorhexidine Gluconate, USP
Formulated for dogs, cats
and horses
Antimicrobial, antibiofilm

16 fl. oz. (473 mL)

Dechra